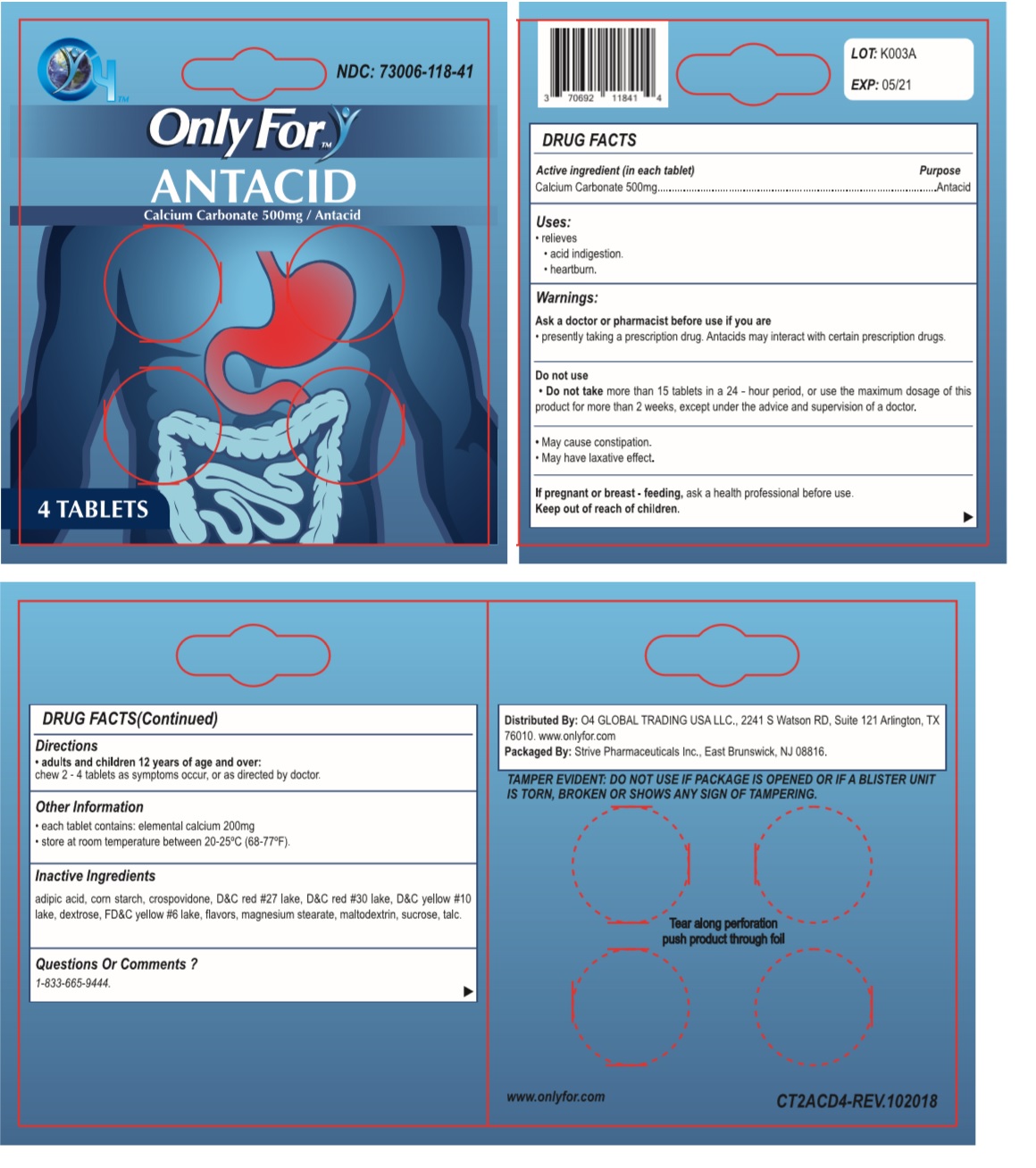 DRUG LABEL: Only For
NDC: 73006-118 | Form: TABLET, CHEWABLE
Manufacturer: O4 Global Trading Usa, Llc 
Category: otc | Type: HUMAN OTC DRUG LABEL
Date: 20190429

ACTIVE INGREDIENTS: CALCIUM CARBONATE 500 mg/1 1
INACTIVE INGREDIENTS: ADIPIC ACID; STARCH, CORN; CROSPOVIDONE, UNSPECIFIED; D&C RED NO. 27 ALUMINUM LAKE; D&C RED NO. 30; D&C YELLOW NO. 10; DEXTROSE MONOHYDRATE; FD&C YELLOW NO. 6; MAGNESIUM PALMITOSTEARATE; MALTODEXTRIN; SUCROSE; TALC

Only For - ANTACID

Active ingredient (in each tablet)

Calcium Carbonate 500mg

Purpose

Antacid

Uses:

• relieves

• acid indigestion.

• heartburn.

Warnings:

Ask a doctor or pharmacist before use if you are

- presently taking a prescription drug. Antacids may interact with certain prescription drugs.

Do not use

- Do not take more than 15 tablets in a 24 - hour period, or use the maximum dosage of this product for more than 2 weeks, except under the advice and supervision of a doctor.

- May cause constipation.
- May have laxative effect.

If pregnant or breast - feeding, ask a health professional before use.

Keep out of reach of children.

Directions

• adults and children 12 years of age and over:

chew 2 - 4 tablets as symptoms occur, or as directed by doctor.

Other Information

- each tablet contains: elemental calcium 200mg
- store at room temperature between 20-25°C (68-77°F).

Inactive Ingredients

adipic acid, corn starch, crospovidone, D&C red #27 lake, D&C red #30 lake, D&C yellow #10 lake, dextrose, FD&C yellow #6 lake, flavors, magnesium stearate, maltodextrin, sucrose, talc.

Questions Or Comments ?

1-833-665-9444.

NDC: 73006-118-41

Distributed By: O4 GLOBAL TRADING USA LLC., 2241 S Watson RD, Suite 121 Arlington, TX 76010.

www.onlyfor.com

Packaged By: Strive Pharmaceuticals Inc., East Brunswick, NJ 08816

TAMPER EVIDENT: DO NOT USE IF PACKAGE IS OPENED OR IF A BLISTER UNIT IS TORN, BROKEN OR SHOWS ANY SIGN OF TAMPERING

Tear along perforation push product through foil